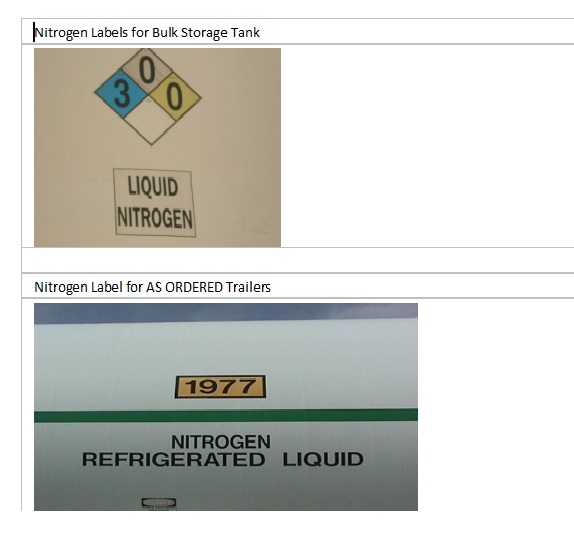 DRUG LABEL: Nitrogen
NDC: 49390-300 | Form: GAS
Manufacturer: Linweld, Inc
Category: prescription | Type: HUMAN PRESCRIPTION DRUG LABEL
Date: 20091120

ACTIVE INGREDIENTS: Nitrogen 99 mL/1 L

Nitrogen label

PACKAGE LABEL

Nitrogen Labels for Bulk Storage Tank

300

LIQUID NITROGEN

Nitrogen Label for AS ORDERED Trailers

1977

NITROGEN REFRIGERATED LIQUID